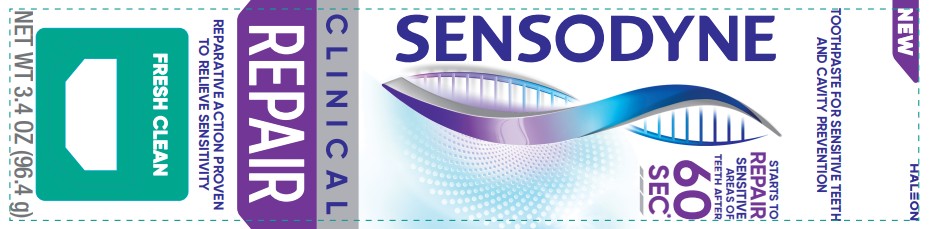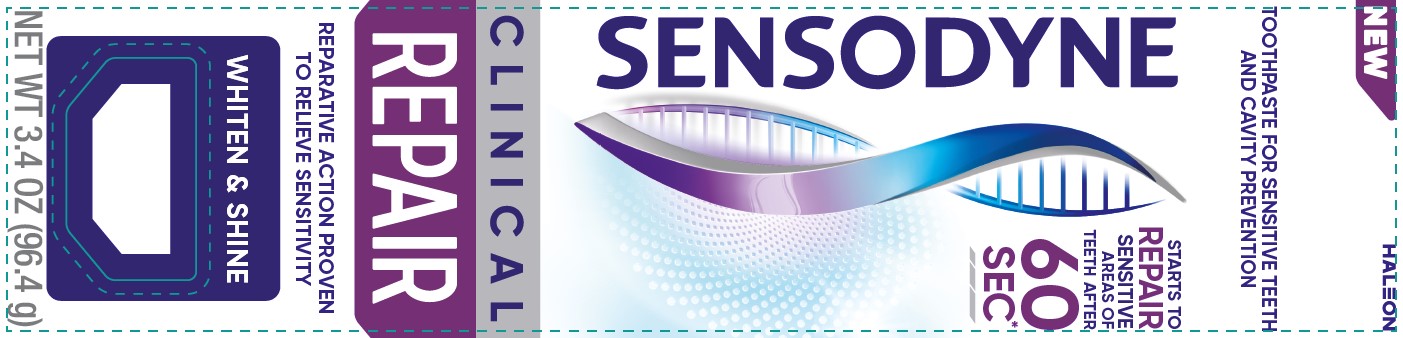 DRUG LABEL: Sensodyne

NDC: 0135-5913 | Form: PASTE, DENTIFRICE
Manufacturer: Haleon US Holdings LLC
Category: otc | Type: HUMAN OTC DRUG LABEL
Date: 20251201

ACTIVE INGREDIENTS: STANNOUS FLUORIDE 15 mg/1 g
INACTIVE INGREDIENTS: GLYCERIN; POLYETHYLENE GLYCOL 400; HYDRATED SILICA; SODIUM TRIPOLYPHOSPHATE ANHYDROUS; PERLITE; SODIUM LAURYL SULFATE; SILICON DIOXIDE; POLYACRYLIC ACID (250000 MW); COCAMIDOPROPYL BETAINE; SACCHARIN SODIUM; BASIC BLUE 1

Drug Facts

Active ingredient

Stannous fluoride 0.454% (0.15% w/v fluoride ion)

Purposes

Anticavity

Antihypersensitivity

Uses

- aids in the prevention of dental cavities.
- builds increasing protection against painful sensitivity of the teeth to cold, heat, acids, sweets, or contact.

Warnings

Stop use and ask a dentist if

- the problem persists or worsens. Sensitive teeth may indicate a serious problem that may need prompt care by a dentist.
- pain/sensitivity still persists after 4 weeks of use.

Keep out of reach of children.

If more than used for brushing is accidentally swallowed, get medical help or contact a Poison Control Center right away.

Directions

- adults and children 12 years of age and older:
  - apply at least a 1-inch strip of the product onto a soft bristle toothbrush.
  - brush teeth thoroughly for at least 1 minute twice a day (morning and evening), and not more than 3 times a day, or as recommended by a dentist or doctor. Make sure to brush all sensitive areas of the teeth. Minimize swallowing. Spit out after brushing.
- children under 12 years of age:Consult a dentist or doctor.

Other information

- products containing stannous fluoride may produce surface staining of the teeth. Adequate toothbrushing may prevent these stains which are not harmful or permanent and may be removed by your dentist.
- this product is specifically formulated to help prevent staining.
- do not store above 30°C (86°F)

Inactive ingredients

glycerin, PEG-8, hydrated silica, pentasodium triphosphate, perlite, flavor, sodium lauryl sulfate, silica, polyacrylic acid, cocamidopropyl betaine, sodium saccharin, blue 1

Questions or comments?

1-866-844-2797

Additional Information (Fresh Clean)

ALWAYS FOLLOW THE LABEL

SENSODYNE

CLINCAL REPAIR

CLINICALLY PROVEN

SENSITIVITY RELIEF

ACTIVATES

Formula activates as soon as you begin to brush your teeth*

REPAIRS

Forms a protective layer inside and over exposed sensitive areas** to block the nerves from sensitivity triggers

PROTECTS

Clinically proven to provide long-lasting sensitivity relief and help prevent the pain from coming back**

SUPERIOR CLEANING ACTION

through stain removal***

Gentle on sensitive teeth

*for substantial sensitivity relief in 3 days

**with continued twice daily brushing

***vs Sensodyne Repair & Protect Deep Repair

Additional Information (Whiten & Shine)

ALWAYS FOLLOW THE LABEL

SENSODYNE

CLINICAL REPAIR

CLINCALLY PROVEN

SENSITIVITY RELIEF

ACTIVATES

Formula activates as soon as you begin to brush your teeth*

REPAIRS

Forms a protective layer inside and over exposed sensitive areas** to block the nerves from sensitivity triggers

PROTECTS

Clinically proven to provide long-lasting sensitivity relief and help prevent the pain from coming back**

SUPERIOR WHITENING ACTION

through stain removal***

Gentle on sensitive teeth

*for substantial sensitivity relief in 3 days

**with continued twice daily brushing

***vs Sensodyne Repair & Protect Deep Repair

Principal Display Panel- Whiten & Shine

NEW

HALEON

TOOTHPASTE FOR SENSITIVE TEETH AND CAVITY PREVENTION

SENSODYNE

STARTS TO REPAIR SENSITIVE AREAS OF THE TEETH AFTER 60 SEC*

CLINICAL REPAIR

REPARATIVE ACTION PROVEN TO RELIEVE SENSITIVITY

WHITEN & SHINE

NET WT 3.4 OZ (96.4 g)

Principal Display Panel- Fresh Clean

NEW

HALEON

TOOTHPASTE FOR SENSTIVE TEETH AND CAVITY PREVENTION

SENSODYNE

STARTS TO REPAIR SENSTIVE AREAS OF TEETH AFTER 60 SEC*

CLINICAL REPAIR

REPARATIVE ACTION PROVEN TO RELIEVE SENSITIVITY

FRESH CLEAN

NET WT 3.4 OZ (96.4 g)